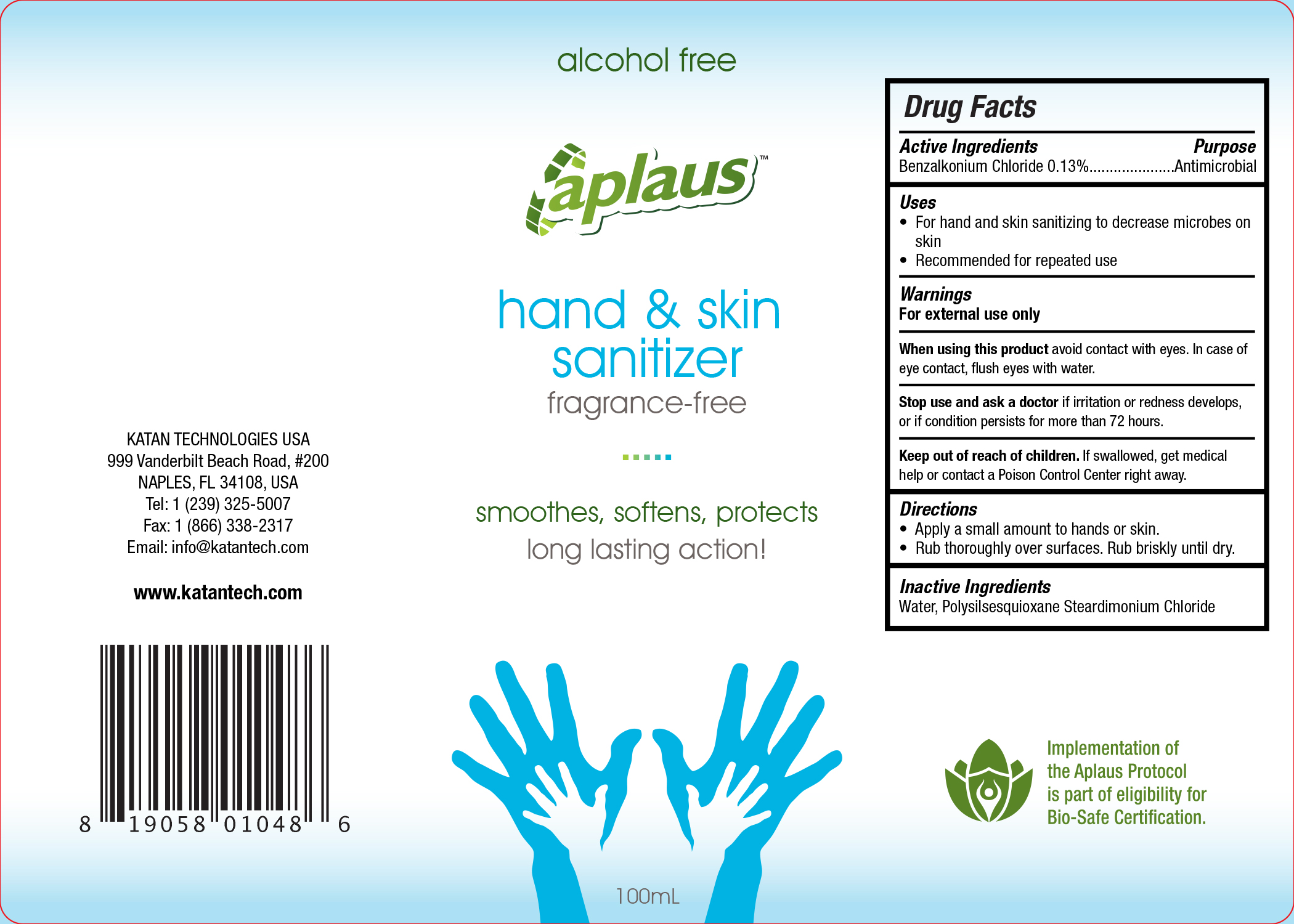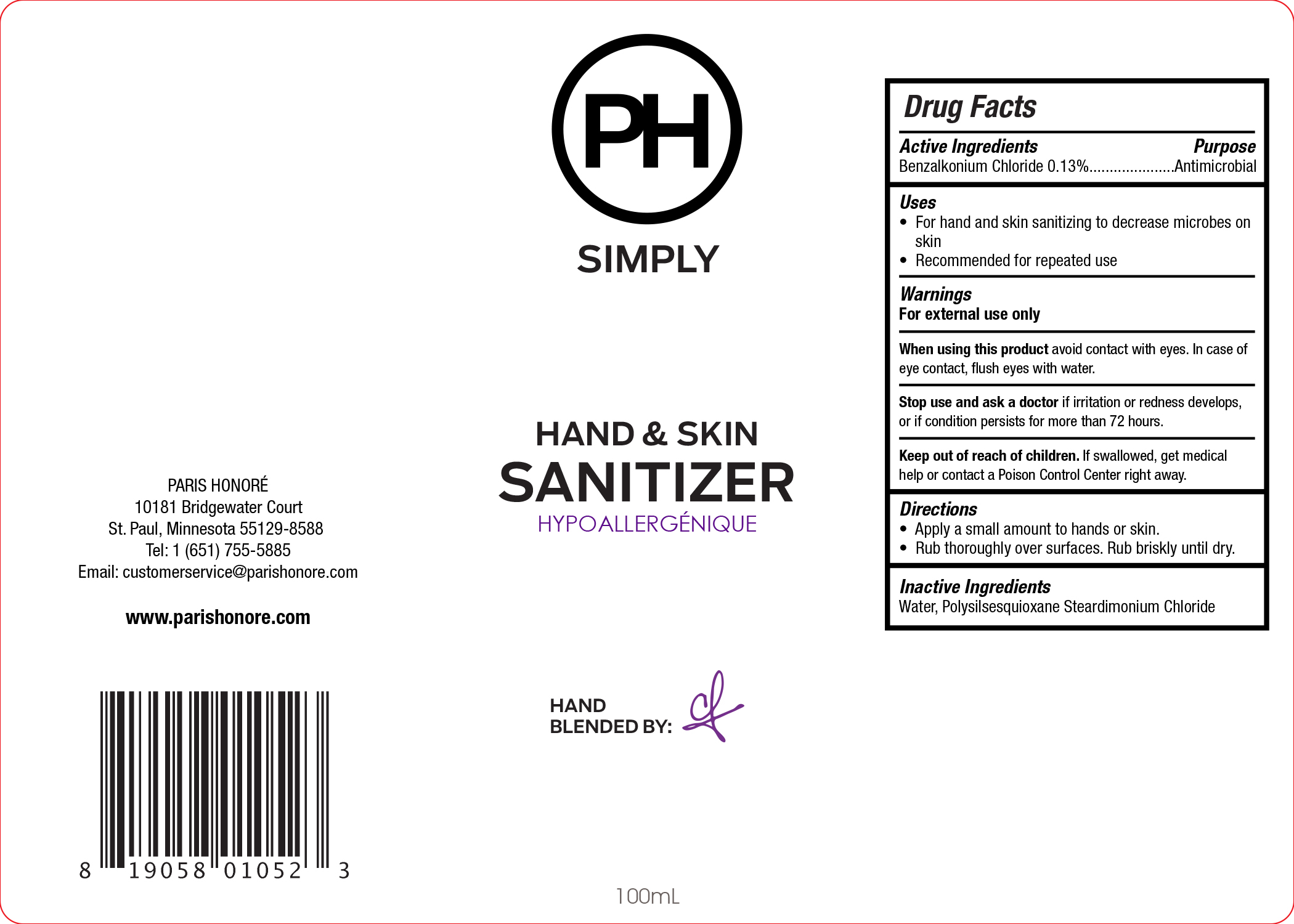 DRUG LABEL: Aplaus Hand and Skin Sanitizer
NDC: 71315-100 | Form: SPRAY
Manufacturer: Katan Technologies USA, LLC
Category: otc | Type: HUMAN OTC DRUG LABEL
Date: 20220113

ACTIVE INGREDIENTS: BENZALKONIUM CHLORIDE 0.13 g/100 mL
INACTIVE INGREDIENTS: DIMETHYLOCTADECYL(3-(TRIMETHOXYSILYL)PROPYL)AMMONIUM CHLORIDE 0.2 g/100 mL; WATER 99.67 mL/100 mL

Aplaus Skin Sanitiser

Active Ingredient

Active Ingredient Purpose

Benzalkonium Chloride 0.1%..................................Antimicrobial

Uses

For hand and skin sanitizing to decrease microbes on skin
Recommended for repeated use

INSTRUCTIONS FOR USE

Apply a small amount to hands or skin.
Rub thoroughly over surfaces. Rub briskly until dry.

Warnings

For external use only.

When using this product avoid contact with eyes. In case of eye contact, flush eyes with water.

Stop use and ask a doctor if irritation or redness develops, or if condition persists for more than 72 hours.

Keep out of reach of children.

If swallowed, get medical help or contact a Poison Control Center right away.

Stop use and ask a doctor if irritation or redness develops, or if condition persists for more than 72 hours.

Inactive Ingredients

Water, Polysilsesquioxane Steardimonium Chloride

Questions

www.parishonore.com

PH Simply Hand & Skin Sanitiser

Drug Facts

Active ingredient Purpose

Benzalkonium Chloride 0.13%..................................Antimicrobial

Uses

•For hand and skin sanitizing
•Recommended for repeated use

Warnings

For external use only

When using this product avoid contact with eyes. In case of eye contact, flush eyes with water.

Stop use and ask a doctor if irritation or redness develops, or if condition persists for more than 72 hours.

Keep out of reach of children. If swallowed, get medical help or contact a Poison Control Center right away.

Directions

•Apply a small amount to hands or skin.
•Rub thoroughly over surfaces. Rub briskly until dry.

Inactive ingredients Water, Polysilsesquioxane Steardimonium Chloride, fragrance